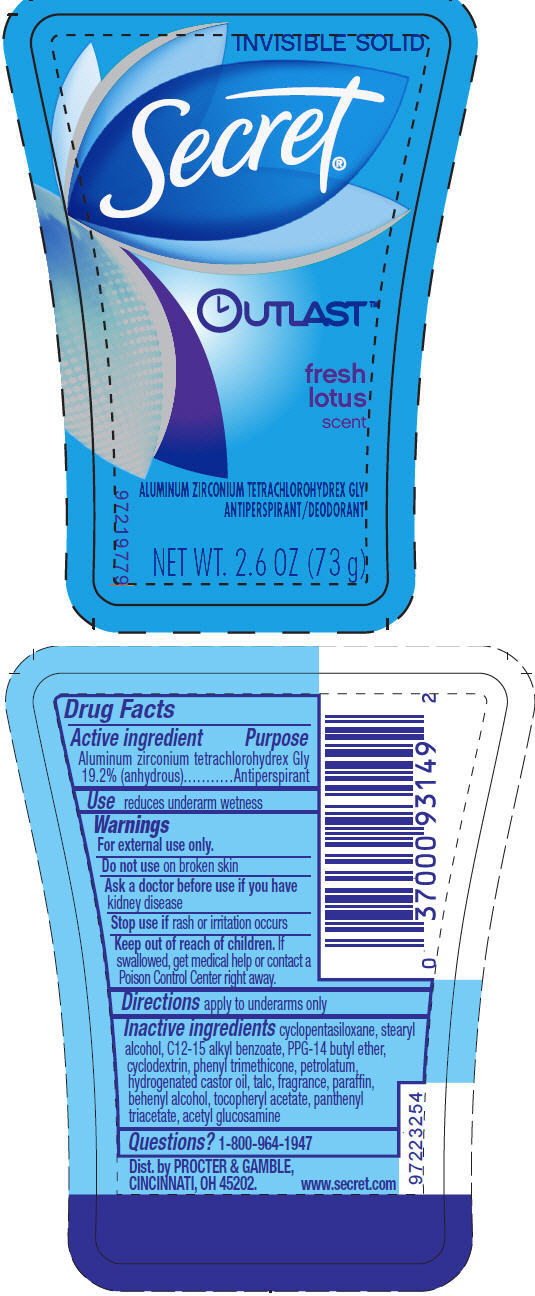 DRUG LABEL: Secret Outlast Invisible Fresh Lotus
NDC: 69423-037 | Form: STICK
Manufacturer: Procter and Gamble Manufacturing Company
Category: otc | Type: HUMAN OTC DRUG LABEL
Date: 20150423

ACTIVE INGREDIENTS: Aluminum Zirconium Tetrachlorohydrex Gly 19.2 g/100 g
INACTIVE INGREDIENTS: CYCLOMETHICONE 5; STEARYL ALCOHOL; ALKYL (C12-15) BENZOATE; PPG-14 BUTYL ETHER; PHENYL TRIMETHICONE; PETROLATUM; HYDROGENATED CASTOR OIL; TALC; PARAFFIN; DOCOSANOL; .ALPHA.-TOCOPHEROL ACETATE; PANTHENOL TRIACETATE, (+)-; N-ACETYLGLUCOSAMINE

Secret® Outlast™ Invisible Fresh Lotus

Drug Facts

Active ingredient

Aluminum zirconium tetrachlorohydrex Gly 19.2% (anhydrous)

Purpose

Antiperspirant

Use

reduces underarm wetness

Warnings

For external use only.

Do not use on broken skin

Ask a doctor before use if you have kidney disease

Stop use if rash or irritation occurs

Keep out of reach of children. If swallowed, get medical help or contact a Poison Control Center right away.

Directions

apply to underarms only

Inactive ingredients

cyclopentasiloxane, stearyl alcohol, C12-15 alkyl benzoate, PPG-14 butyl ether, cyclodextrin, phenyl trimethicone, petrolatum, hydrogenated castor oil, talc, fragrance, paraffin, behenyl alcohol, tocopheryl acetate, panthenyl triacetate, acetyl glucosamine

Questions?

1-800-964-1947

Dist. by PROCTER & GAMBLE,
CINCINNATI, OH 45202.

PRINCIPAL DISPLAY PANEL - 73 g Cylinder Label

INVISIBLE SOLID

Secret®

OUTLAST™

fresh
lotus
scent

ALUMINUM ZIRCONIUM TETRACHLOROHYDREX GLY
ANTIPERSPIRANT/DEODORANT

NET WT. 2.6 OZ (73 g)

97219779